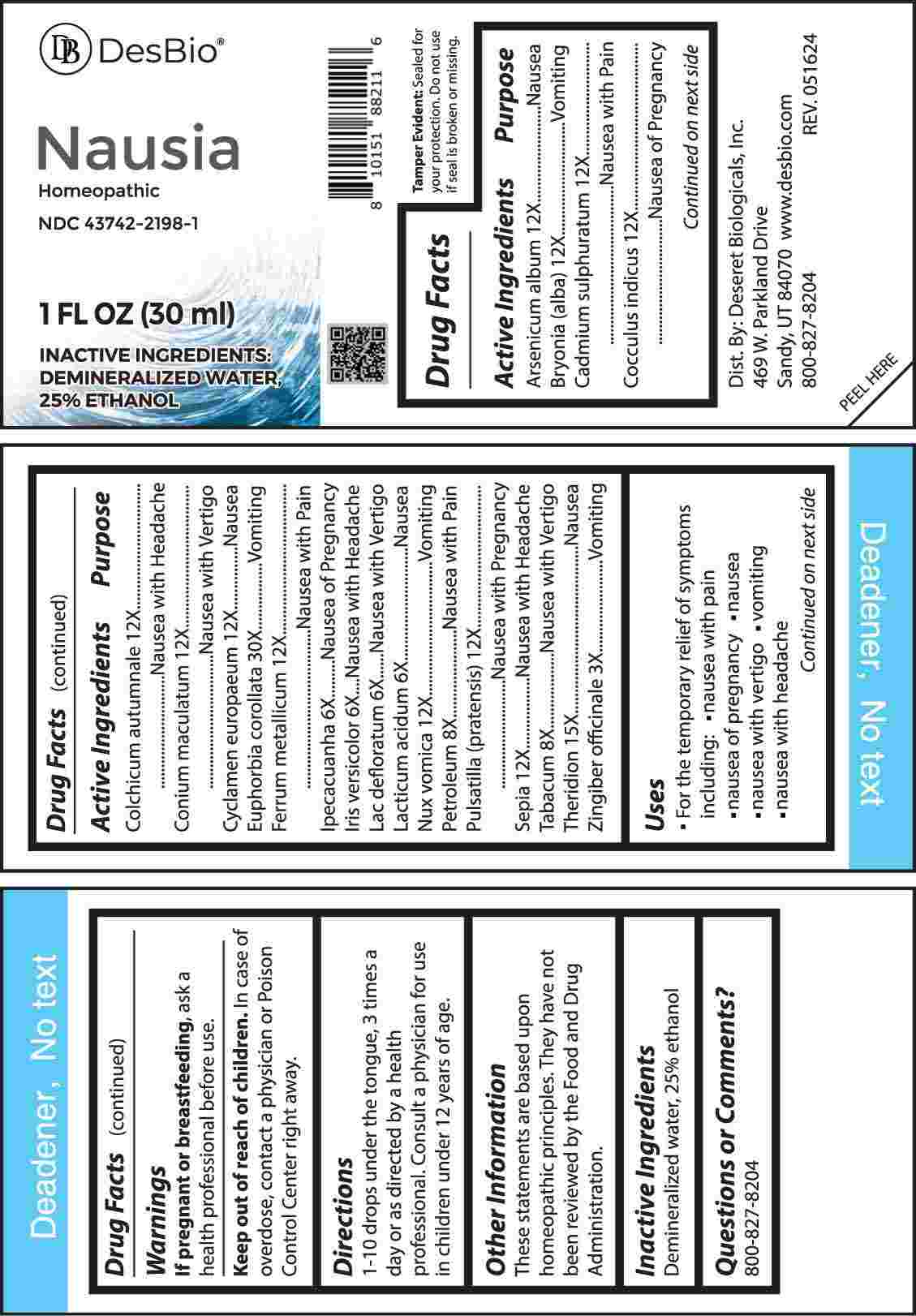 DRUG LABEL: Nausia
NDC: 43742-2198 | Form: LIQUID
Manufacturer: Deseret Biologicals, Inc.
Category: homeopathic | Type: HUMAN OTC DRUG LABEL
Date: 20240923

ACTIVE INGREDIENTS: ARSENIC TRIOXIDE 12 [hp_X]/1 mL; BRYONIA ALBA ROOT 12 [hp_X]/1 mL; CADMIUM SULFIDE 12 [hp_X]/1 mL; ANAMIRTA COCCULUS SEED 12 [hp_X]/1 mL; COLCHICUM AUTUMNALE BULB 12 [hp_X]/1 mL; CONIUM MACULATUM FLOWERING TOP 12 [hp_X]/1 mL; CYCLAMEN PURPURASCENS TUBER 12 [hp_X]/1 mL; EUPHORBIA COROLLATA ROOT 30 [hp_X]/1 mL; IRON 12 [hp_X]/1 mL; IPECAC 6 [hp_X]/1 mL; IRIS VERSICOLOR ROOT 6 [hp_X]/1 mL; SKIM MILK 6 [hp_X]/1 mL; LACTIC ACID, DL- 6 [hp_X]/1 mL; STRYCHNOS NUX-VOMICA SEED 12 [hp_X]/1 mL; KEROSENE 8 [hp_X]/1 mL; PULSATILLA PRATENSIS WHOLE 12 [hp_X]/1 mL; SEPIA OFFICINALIS JUICE 12 [hp_X]/1 mL; TOBACCO LEAF 8 [hp_X]/1 mL; THERIDION CURASSAVICUM 15 [hp_X]/1 mL; GINGER 3 [hp_X]/1 mL
INACTIVE INGREDIENTS: WATER; ALCOHOL

DRUG FACTS:

ACTIVE INGREDIENTS:

Arsenicum Album 12X, Bryonia (Alba) 12X, Cadmium Sulphuratum 12X, Cocculus Indicus 12X, Colchicum Autumnale 12X, Conium Maculatum 12X, Cyclamen Europaeum 12X, Euphorbia Corollata 30X, Ferrum Metallicum 12X, Ipecacuanha 6X, Iris Versicolor 6X, Lac Defloratum 6X, Lacticum Acidum 6X, Nux Vomica 12X, Petroleum 8X, Pulsatilla (Pratensis) 12X, Sepia 12X, Tabacum 8X, Theridion 15X, Zingiber Officinale 3X.

PURPOSE:

Arsenicum Album - Nausea, Bryonia (Alba) - Vomiting, Cadmium Sulphuratum – Nausea with Pain, Cocculus Indicus – Nausea of Pregnancy, Colchicum Autumnale – Nausea with Headache, Conium Maculatum – Nausea with Vertigo, Cyclamen Europaeum - Nausea, Euphorbia Corollata - Vomiting, Ferrum Metallicum – Nausea with Pain, Ipecacuanha – Nausea of Pregnancy, Iris Versicolor – Nausea with Headache, Lac Defloratum – Nausea with Vertigo, Lacticum Acidum - Nausea, Nux Vomica - Vomiting, Petroleum – Nausea with Pain, Pulsatilla (Pratensis) – Nausea with Pregnancy, Sepia – Nausea with Headache, Tabacum – Nausea with Vertigo, Theridion - Nausea, Zingiber Officinale - Vomiting

USES:

• For the temporary relief of the symptoms including:

• nausea with pain • nausea with pregnancy • nausea

• nausea with vertigo • vomiting • nausea with headache

These statements are based upon homeopathic principles. They have not been reviewed by the Food and Drug Administration.

WARNINGS:

If pregnant or breast-feeding, ask a health professional before use.

Keep out of reach of children. In case of overdose, contact a physician or Poison Control Center right away.

Tamper Evident: Sealed for your protection. Do not use if seal is broken or missing.

KEEP OUT OF REACH OF CHILDREN:

In case of overdose, contact a physician or Poison Control Center right away.

DIRECTIONS:

1-10 drops under the tongue, 3 times a day or as directed by a health professional. Consult a physician for use in children under 12 years of age.

INACTIVE INGREDIENTS:

Demineralized water, 25% ethanol

QUESTIONS:

Dist. By: Deseret Biologicals, Inc.
469 W. Parkland Drive
Sandy, UT 84070

www.desbio.com

800-827-8204

PACKAGE LABEL DISPLAY:

DesBio

Nausia

Homeopathic
NDC 43742-2198-1
1 FL OZ (30 ml)